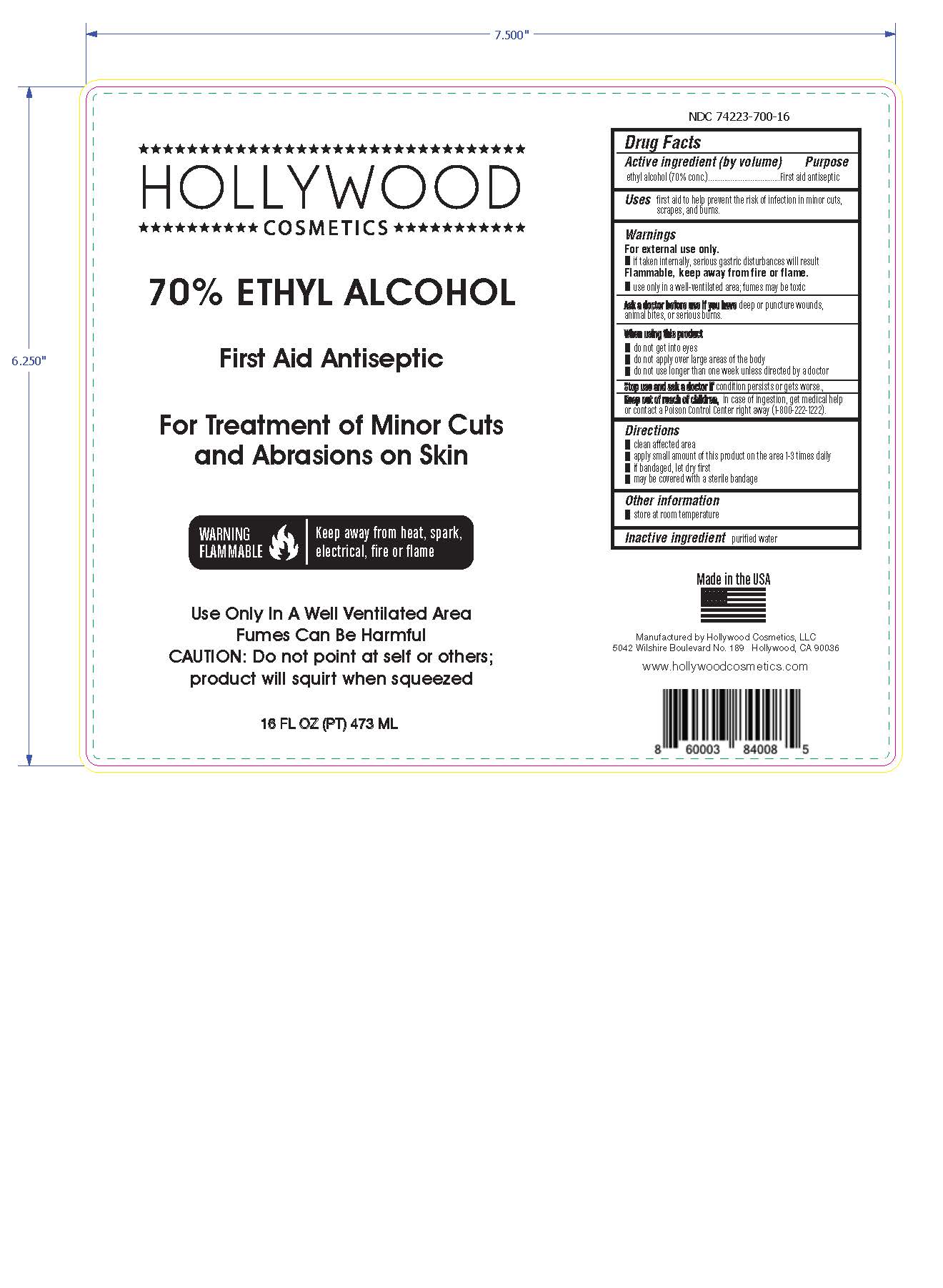 DRUG LABEL: Hollywood Cosmetics 70% Ethyl Alcohol
NDC: 74223-700 | Form: LIQUID
Manufacturer: Hollywood Cosmetics, LLC
Category: otc | Type: HUMAN OTC DRUG LABEL
Date: 20201005

ACTIVE INGREDIENTS: ALCOHOL 70 mL/100 mL
INACTIVE INGREDIENTS: WATER

Active Ingredient(s)

Alcohol 70% v/v. Purpose: First Aid Antiseptic

Purpose

First Aid Antiseptic

Use

First aid to to help prevent the risk of infection in minor cuts, scrapes and burns.

Warnings

For external use only.

If taken internally, serious gastric disturbances will result

Flammable, keep away from fire or flame

Use only in a well-ventilated area, fumes may be toxic

When using this product:

- Do not get into eyes
- Do not apply over large areas of the body
- Do not use longer than one week unless directed by a doctor

Keep out of reach of children. In case of ingestion, get medical help or contact a Poison Control Center right away (800-222-1222)

Directions

- Clean affected area
- apply small amount of this product on the area 1-3 times daily
- if bandaged, let dry first
- may be covered with a sterile bandage

Other information

- Store at room temperature

Inactive ingredients

purified water

Ask a doctor before use if you have deep puncture wounds, animal bites or serious burns.

Stop use and ask a doctor if condition persists or gets worse

PACKAGE LABEL

473 mL NDC: 74223-700-16